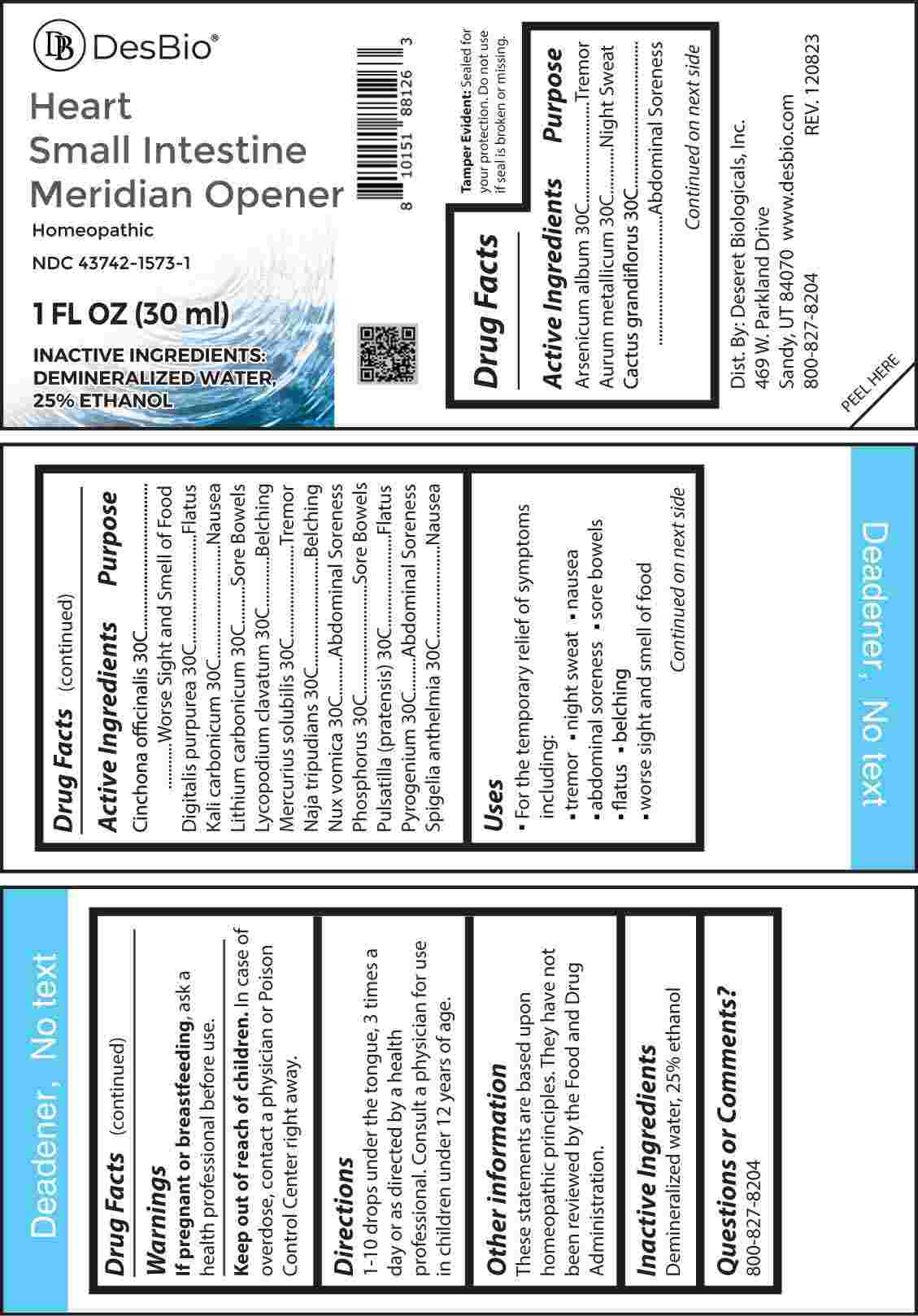 DRUG LABEL: Heart Small Intestine Meridian Opener
NDC: 43742-1573 | Form: LIQUID
Manufacturer: Deseret Biologicals, Inc.
Category: homeopathic | Type: HUMAN OTC DRUG LABEL
Date: 20250527

ACTIVE INGREDIENTS: ARSENIC TRIOXIDE 30 [hp_C]/1 mL; GOLD 30 [hp_C]/1 mL; ATROPA BELLADONNA 30 [hp_C]/1 mL; SELENICEREUS GRANDIFLORUS STEM 30 [hp_C]/1 mL; CINCHONA OFFICINALIS BARK 30 [hp_C]/1 mL; DIGITALIS 30 [hp_C]/1 mL; POTASSIUM CARBONATE 30 [hp_C]/1 mL; LITHIUM CARBONATE 30 [hp_C]/1 mL; LYCOPODIUM CLAVATUM SPORE 30 [hp_C]/1 mL; MERCURIUS SOLUBILIS 30 [hp_C]/1 mL; NAJA NAJA VENOM 30 [hp_C]/1 mL; STRYCHNOS NUX-VOMICA SEED 30 [hp_C]/1 mL; PHOSPHORUS 30 [hp_C]/1 mL; PULSATILLA PRATENSIS WHOLE 30 [hp_C]/1 mL; RANCID BEEF 30 [hp_C]/1 mL; SPIGELIA ANTHELMIA WHOLE 30 [hp_C]/1 mL
INACTIVE INGREDIENTS: WATER; ALCOHOL

DRUG FACTS:

ACTIVE INGREDIENTS:

Arsenicum Album 30C, Aurum Metallicum 30C, Cactus Grandiflorus 30C, Cinchona Officinalis 30C, Digitalis Purpurea 30C, Kali Carbonicum 30C, Lithium Carbonicum 30C, Lycopodium Clavatum 30C, Mercurius Solubilis 30C, Naja Tripudians 30C, Nux Vomica 30C, Phosphorus 30C, Pulsatilla (Pratensis) 30C, Pyrogenium 30C, Spigelia Anthelmia 30C.

PURPOSE:

Arsenicum Album - Tremor, Aurum Metallicum – Night Sweat, Cactus Grandiflorus – Abdominal Soreness, Cinchona Officinalis – Worse Sight and Smell of Food, Digitalis Purpurea - Flatus, Kali Carbonicum - Nausea, Lithium Carbonicum – Sore Bowels, Lycopodium Clavatum - Belching, Mercurius Solubilis - Tremor, Naja Tripudians - Belching, Nux Vomica – Abdominal Soreness, Phosphorus – Sore Bowels, Pulsatilla (Pratensis) - Flatus, Pyrogenium – Abdominal Soreness, Spigelia Anthelmia - Nausea

USES:

• For the temporary relief of symptoms including:

• tremor • night sweat • nausea • abdominal soreness

• sore bowels • flatus • belching • worse sight and smell of food

These statements are based upon homeopathic principles. They have not been reviewed by the Food and Drug Administration.

WARNINGS:

If pregnant or breast-feeding, ask a health professional before use.

Keep out of reach of children. In case of overdose, contact a physician or Poison Control Center right away.

Tamper Evident: Sealed for Your Protection. Do not use if seal is broken or missing.

KEEP OUT OF REACH OF CHILDREN:

In case of overdose, contact a physician or Poison Control Center right away.

DIRECTIONS:

1-10 drops under the tongue, 3 times a day or as directed by a health professional. Consult a physician for use in children under 12 years of age.

INACTIVE INGREDIENTS:

Demineralized water, 25% ethanol

QUESTIONS:

Dist. By: Deseret Biologicals, Inc.

469 W. Parkland Drive

Sandy, UT 84070

www.desbio.co

800-827-8204

PACKAGE LABEL DISPLAY:

Des Bio

Heart Small Intestine

Meridian Opener

Homeopathic

NDC 43742-1573-1

1 FL OZ (30 ml)